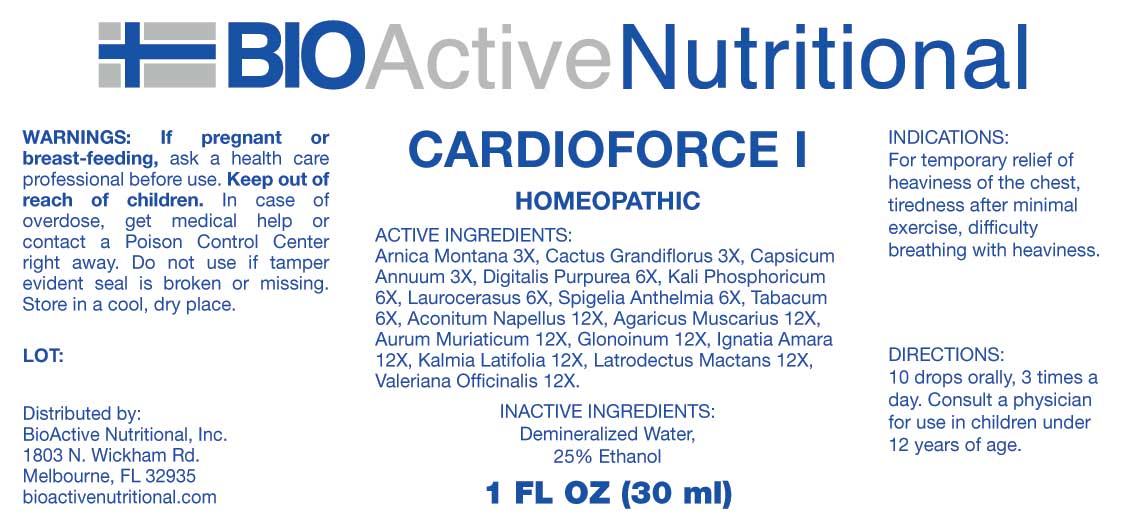 DRUG LABEL: Cardioforce
NDC: 43857-0652 | Form: LIQUID
Manufacturer: BioActive Nutritional, Inc.
Category: homeopathic | Type: HUMAN OTC DRUG LABEL
Date: 20250102

ACTIVE INGREDIENTS: ARNICA MONTANA WHOLE 3 [hp_X]/1 mL; SELENICEREUS GRANDIFLORUS STEM 3 [hp_X]/1 mL; CAPSICUM 3 [hp_X]/1 mL; DIGITALIS 6 [hp_X]/1 mL; DIBASIC POTASSIUM PHOSPHATE 6 [hp_X]/1 mL; PRUNUS LAUROCERASUS LEAF 6 [hp_X]/1 mL; SPIGELIA ANTHELMIA WHOLE 6 [hp_X]/1 mL; TOBACCO LEAF 6 [hp_X]/1 mL; ACONITUM NAPELLUS WHOLE 12 [hp_X]/1 mL; AMANITA MUSCARIA FRUITING BODY 12 [hp_X]/1 mL; GOLD TRICHLORIDE 12 [hp_X]/1 mL; NITROGLYCERIN 12 [hp_X]/1 mL; STRYCHNOS IGNATII SEED 12 [hp_X]/1 mL; KALMIA LATIFOLIA LEAF 12 [hp_X]/1 mL; LATRODECTUS MACTANS 12 [hp_X]/1 mL; VALERIAN 12 [hp_X]/1 mL
INACTIVE INGREDIENTS: WATER; ALCOHOL

DRUG FACTS:

ACTIVE INGREDIENTS:

Arnica Montana 3X, Cactus Grandiflorus 3X, Capsicum Annuum 3X, Digitalis Purpurea 6X, Kali Phosphoricum 6X, Laurocerasus 6X, Spigelia Anthelmia 6X, Tabacum 6X, Aconitum Napellus 12X, Agaricus Muscarius 12X, Aurum Muriaticum 12X, Glonoinum 12X, Ignatia Amara 12X, Kalmia Latifolia 12X, Latrodectus Mactans 12X, Valeriana Officinalis 12X.

PURPOSE:

For temporary relief of heaviness of the chest, tiredness after minimal exercise, difficulty breathing with heaviness.

WARNINGS:

If pregnant or breast-feeding, ask a health care professional before use.

Keep out of reach of children. In case of overdose, get medical help or contact a Poison Control Center right away.

Do not use if tamper evident seal is broken or missing.

Store in a cool, dry place.

KEEP OUT OF REACH OF CHILDREN:

In case of overdose, get medical help or contact a Poison Control Center right away.

DIRECTIONS:

10 drops orally, 3 times a day. Consult a physician for use in children under 12 years of age.

INDICATIONS:

For temporary relief of heaviness of the chest, tiredness after minimal exercise, difficulty breathing with heaviness.

INACTIVE INGREDIENTS:

Demineralized Water, 25% Ethanol

QUESTIONS:

Distributed by:

BioActive Nutritional, Inc.

1803 N. Wickham Rd.

Melbourne, FL 32935

bioactivenutritional.com

PACKAGE LABEL DISPLAY:

BIOActiveNutritional

CARDIOFORCE I

HOMEOPATHIC

1 FL OZ (30 ml)